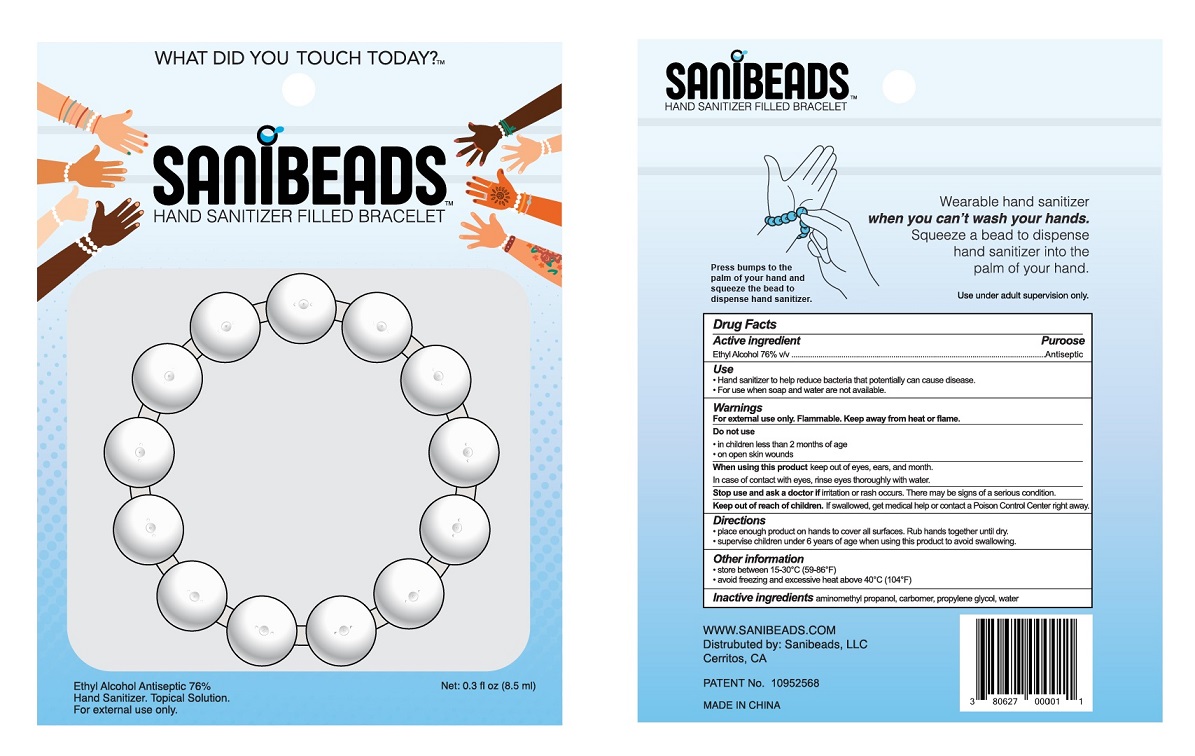 DRUG LABEL: Sanibeads
NDC: 80627-001 | Form: GEL
Manufacturer: SANIBEADS, LLC
Category: otc | Type: HUMAN OTC DRUG LABEL
Date: 20220118

ACTIVE INGREDIENTS: ALCOHOL 76 mL/100 mL
INACTIVE INGREDIENTS: PROPYLENE GLYCOL; CARBOMER COPOLYMER TYPE A (ALLYL PENTAERYTHRITOL CROSSLINKED); WATER; AMINOMETHYLPROPANOL

Active Ingredient

Ethyl Alcohol 76% v/v.

Purpose

Antiseptic

Use

Hand Sanitizer to help reduce bacteria that potentially can cause disease. For use when soap and water are not available.

Warnings

For external use only. Flammable. Keep away from heat or flame

Do not use

- in children less than 2 months of age
- on open skin wounds

When using this product keep out of eyes, ears, and mouth. In case of contact with eyes, rinse eyes thoroughly with water.
Stop use and ask a doctor if irritation or rash occurs. These may be signs of a serious condition.

Keep out of reach of children. If swallowed, get medical help or contact a Poison Control Center right away.

Directions

- Place enough product on hands to cover all surfaces. Rub hands together until dry.
- Supervise children under 6 years of age when using this product to avoid swallowing.

Other information

- Store between 15-30°C (59-86°F)
- Avoid freezing and excessive heat above 40°C (104°F)

Inactive ingredients

Aminomethyl propanol, Carbomer, propylene glycol, water